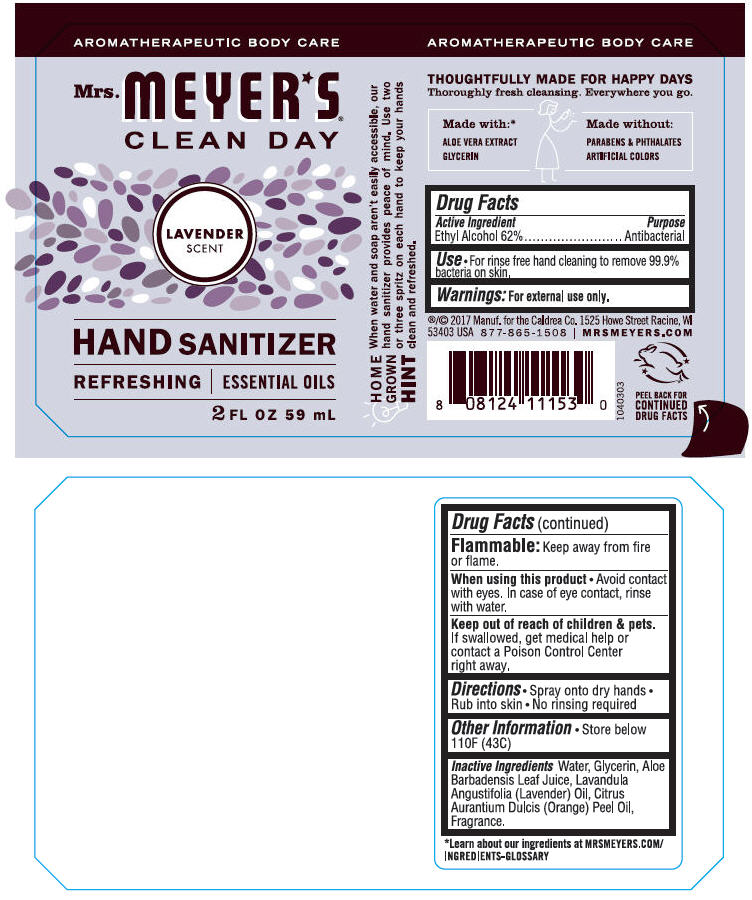 DRUG LABEL: Mrs. Meyers Clean Day Hand Sanitizer Lavender Scent
NDC: 71763-201 | Form: SOLUTION
Manufacturer: The Caldrea Company
Category: otc | Type: HUMAN OTC DRUG LABEL
Date: 20251204

ACTIVE INGREDIENTS: ALCOHOL 0.62 mL/1 mL
INACTIVE INGREDIENTS: WATER; GLYCERIN; ALOE VERA LEAF; LAVENDER OIL; ORANGE OIL, COLD PRESSED

MRS. MEYER'S® CLEAN DAY HAND SANITIZER LAVENDER SCENT

Drug Facts

Active Ingredient

Ethyl Alcohol 62%

Purpose

Antibacterial

Use

- For rinse free hand cleaning to remove 99.9% bacteria on skin.

Warnings

For external use only.

Flammable

Keep away from fire or flame.

When using this product

- Avoid contact with eyes. In case of eye contact, rinse with water.

Keep out of reach of children & pets. If swallowed, get medical help or contact a Poison Control Center right away.

Directions

- Spray onto dry hands
- Rub into skin
- No rinsing required

Other Information

- Store below 110F (43C)

Inactive Ingredients

Water, Glycerin, Aloe Barbadensis Leaf Juice, Lavandula Angustifolia (Lavender) Oil, Citrus Aurantium Dulcis (Orange) Peel Oil, Fragrance.

PRINCIPAL DISPLAY PANEL - 59 mL Bottle Label

AROMATHERAPEUTIC BODY CARE

Mrs.
MEYER⋆S®
CLEAN DAY

LAVENDER
SCENT

HAND SANITIZER

REFRESHING | ESSENTIAL OILS

2 FL OZ 59 mL